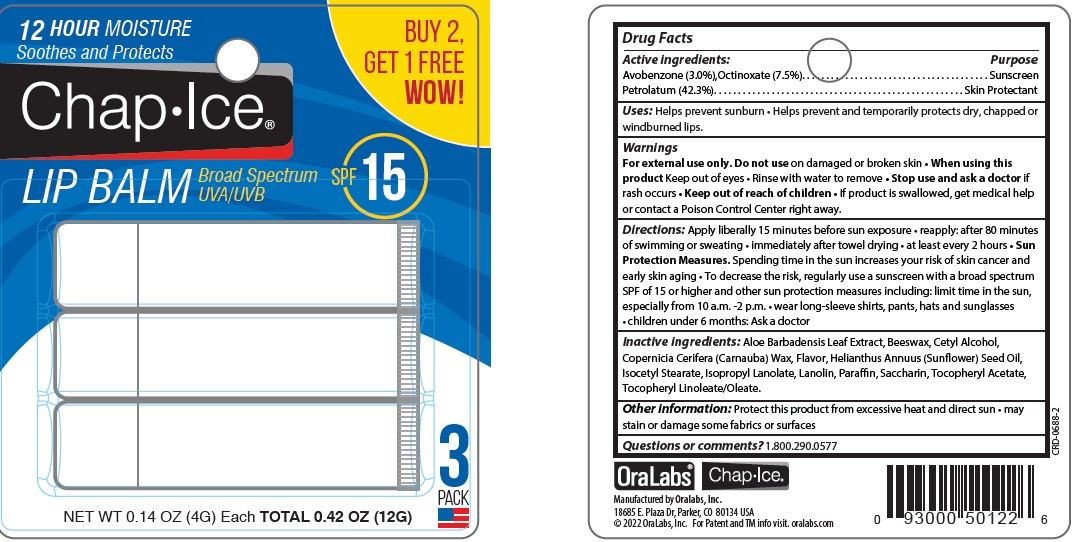 DRUG LABEL: OraLabs SPF 15 Lip Balm
NDC: 63645-181 | Form: STICK
Manufacturer: OraLabs
Category: otc | Type: HUMAN OTC DRUG LABEL
Date: 20250422

ACTIVE INGREDIENTS: OCTINOXATE 75 mg/1 g; AVOBENZONE 30 mg/1 g; PETROLATUM 423 mg/1 g
INACTIVE INGREDIENTS: PARAFFIN 230 mg/1 g; ISOCETYL STEARATE 140 mg/1 g; LANOLIN 10 mg/1 g; .ALPHA.-TOCOPHEROL ACETATE 10 mg/1 g

Drug Facts

Active ingredient

Avobenzone (3.0%), Octinoxate (7.5%)

Petrolatum (42.3%)

Purpose

Sunscreen, Sunscreen, Skin Protectant

Keep Out of Reach of Children

If swallowed get medical help or contact a Poison Control Center right away.

Uses

Helps prevent sunburn. if used as directed with other sun protection measures (see Directions) decreases the risk of skin cancer and early aging caused by the sun. helps prevent and temporarily protects chafed, chapped or cracked lips. Helps prevent and protect from the drying effects of wind and cold weather

Warnings

For external use only: Do not use on damaged or broken skin. When using this product. Keep out of eyes. Rinse with water to remove. Stop use and ask a doctor: if rash occurs

Directions

Apply liberally 15 minutes before sun exposure. Reapply: after 80 minutes of swimming or sweating. Immediately after towel drying. At least every 2 hours. Sun Protection Measures. Spending time in the sun increases your risk of skin cancer and early skin aging. To decrease the risk, regularly use a sunscreen with a broad spectrum SPF of 15 or higher and other sun protection measures including: limit time in the sun, especially from 10 a.m. to 2 p.m. wear long-sleeve shirts, pants, hats and sunglasses. Children under 6 months: Ask a doctor.

Inactive Ingredients

Aloe Barbadensis Leaf Extract, Beeswax, Cetyl Alcohol, Copernicia Cerifera (Carnauba) Wax, Flavor, Helianthus Annuus (Sunflower) Seed Oil, Isocetyl Stearate, Isopropyl Lanolate, Lanolin, Parraffin, Saccharin, Tocopheryl Acetate, Tocerpheryl Linoleate/Oleate.